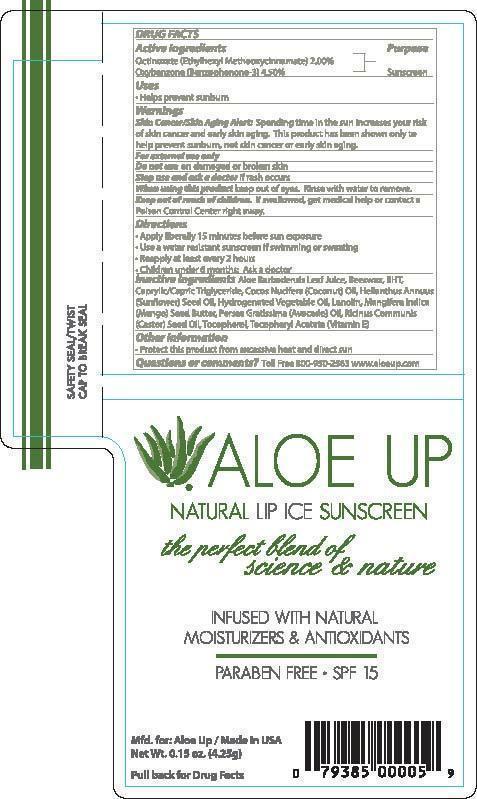 DRUG LABEL: ALOE UP NATURAL LIP ICE SUNSCREEN
NDC: 61477-214 | Form: LIPSTICK
Manufacturer: Aloe Care International, LLC
Category: otc | Type: HUMAN OTC DRUG LABEL
Date: 20240213

ACTIVE INGREDIENTS: OCTINOXATE 2 g/100 g; OXYBENZONE 4.5 g/100 g
INACTIVE INGREDIENTS: TOCOPHEROL; YELLOW WAX; BUTYLATED HYDROXYTOLUENE; MEDIUM-CHAIN TRIGLYCERIDES; COCONUT OIL; SUNFLOWER OIL; HYDROGENATED SOYBEAN OIL; LANOLIN; MANGIFERA INDICA SEED BUTTER; AVOCADO OIL; CASTOR OIL; .ALPHA.-TOCOPHEROL ACETATE; ALOE VERA LEAF

ALOE UP - NATURAL LIP ICE SPF 15 (61477-214)

ACTIVE INGREDIENTS:

OCTINOXATE (%)

OXYBENZONE (4.5%)

PURPOSE:

SUNSCREEN

INDICATIONS:

HELPS PREVENT SUNBURN.

DIRECTIONS:

APPLY LIBERALLY 15 MINUTES BEFORE SUN EXPOSURE.

USE A WATER RESISTANT SUNSCREEN IF SWIMMING OR SWEATING.

REAPPLY AT LEAST EVERY 2 HOURS.

CHILDREN UNDER 6 MONTHS: ASK A DOCTOR.

KEEP OUT OF REACH OF CHILDREN.

WARNINGS:

FOR EXTERNAL USE ONLY. DO NOT USE ON DAMAGED OR BROKEN SKIN. WHEN USING THIS PRODUCT KEEP OUT OF EYES. RINSE WITH WATER TO REMOVE. STOP USE AND ASK A DOCTOR IF RASH OCCURS. KEEP OUT OF REACH OF CHILDREN. IF SWALLOWED, GET MEDICAL HELP OR CONTACT A POISON CONTROL CENTER RIGHT AWAY.

INACTIVE INGREDIENT

Other Ingredients:

ALOE BARBADENSIS LEAF JUICE, BEESWAX, BHT, CAPRYLIC/CAPRIC TRIGLYCERIDE, COCOS NUCIFERA (COCONUT) OIL, HELIANTHUS ANNUUS (SUNFLOWER) SEED OIL, HYDROGENATED VEGETABLE OIL, LANOLIN, MANGIFERA INDICA (MANGO) SEED BUTTER, PERSEA GRATISSIMA (AVOCADO) OIL, RICINUS COMMUNIS (CASTOR) SEED OIL, TOCOPHEROL, TOCOPHERYL ACETATE (VITAMIN E)